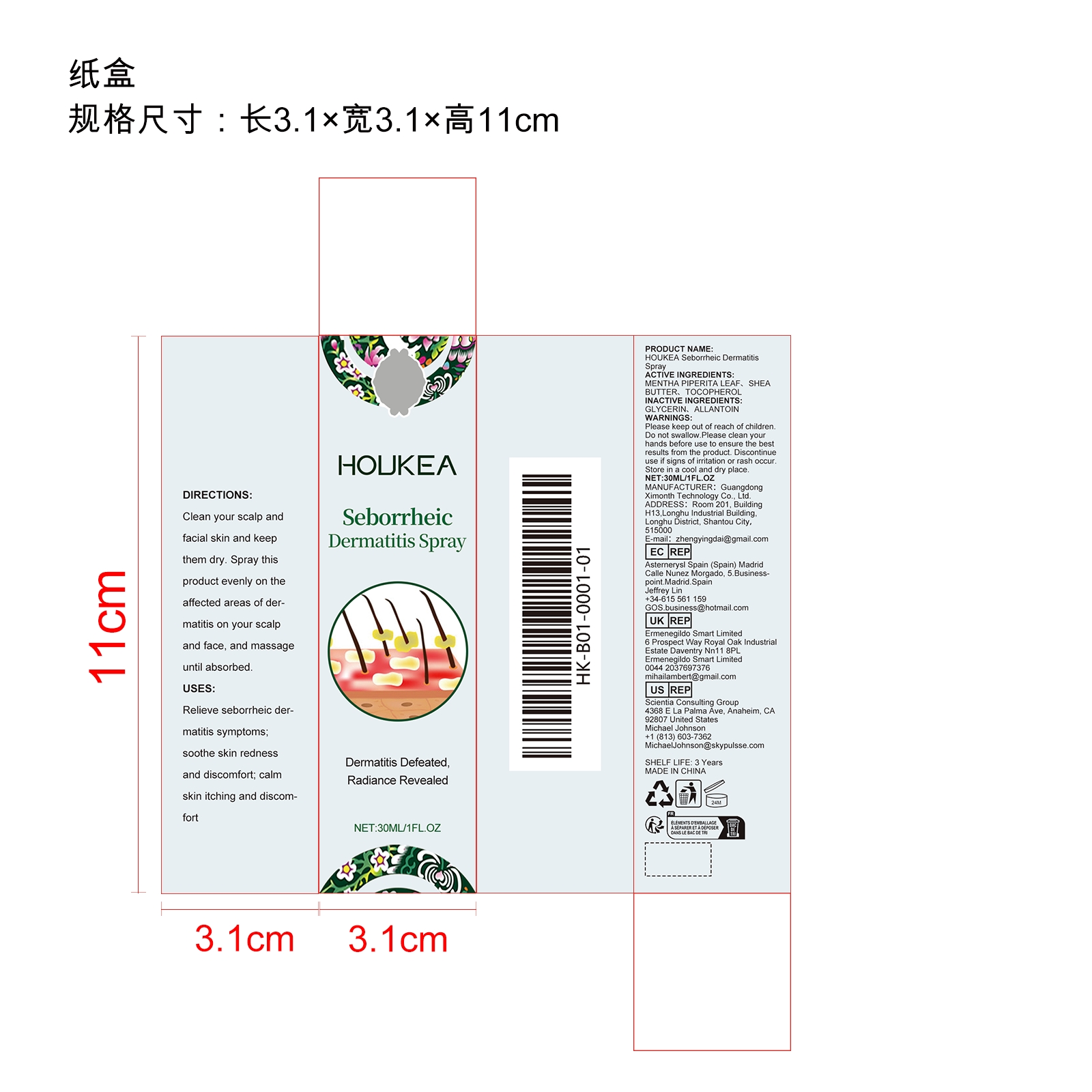 DRUG LABEL: HOUKEA Seborrheic Dermatitis
NDC: 84660-096 | Form: SPRAY
Manufacturer: Guangdong Ximonth Technology Co., Ltd.
Category: otc | Type: HUMAN OTC DRUG LABEL
Date: 20241029

ACTIVE INGREDIENTS: MENTHA PIPERITA LEAF 9 g/30 g; SHEA BUTTER 3 g/30 g; TOCOPHEROL 4.5 g/30 g
INACTIVE INGREDIENTS: GLYCERIN 4.5 g/30 g; ALLANTOIN 9 g/30 g

ACTIVE INGREDIENTS

MENTHA PIPERITA LEAF、SHEA BUTTER、TOCOPHEROL

PURPOSE

Relieve seborrheic dermatitis symptoms; soothe skin redness and discomfort; calm skin itching and discomfort

USES

Clean your scalp and facial skin and keep them dry. Spray this product evenly on the affected areas of dermatitis on your scalp and face, and massage until absorbed.

WARNINGS

Please keep out of reach of children. Do not swallow.Please clean your hands before use to ensure the best results from the product. Discontinue use if signs of irritation or rash occur. Store in a cool and dry place.

STOP USE

Discontinue use if signs of irritation or rash occur.

DO NOT USE

Discontinue use if signs of irritation or rash occur.

KEEP OUT OF REACH OF CHILDREN

Please keep out of reach of children. Do not swallow.

STORAGE AND HANDLING

Store in a cool and dry place.

INACTIVE INGREDIENT

GLYCERIN、ALLANTOIN